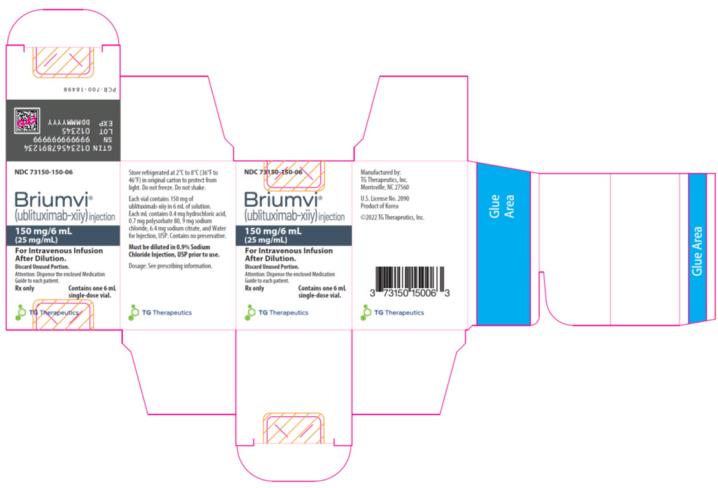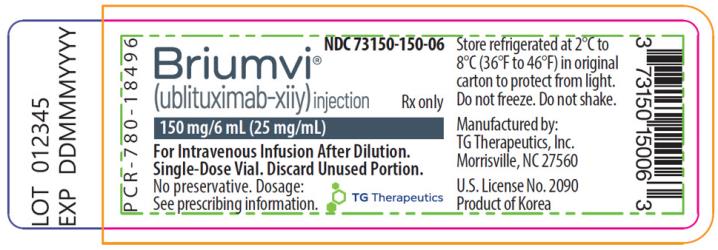 DRUG LABEL: BRIUMVI
NDC: 73150-150 | Form: INJECTION, SOLUTION, CONCENTRATE
Manufacturer: TG Therapeutics, Inc.
Category: prescription | Type: HUMAN PRESCRIPTION DRUG LABEL
Date: 20260219

ACTIVE INGREDIENTS: UBLITUXIMAB 150 mg/6 mL
INACTIVE INGREDIENTS: SODIUM CHLORIDE; SODIUM CITRATE, UNSPECIFIED FORM; POLYSORBATE 80; HYDROCHLORIC ACID; WATER

HIGHLIGHTS OF PRESCRIBING INFORMATION

These highlights do not include all the information needed to use BRIUMVI safely and effectively. See full prescribing information for BRIUMVI.
BRIUMVI®(ublituximab-xiiy) injection, for intravenous use
Initial U.S. Approval: 2022

RECENT MAJOR CHANGES

Dosage and Administration (2.1, 2.2) | 8/2025
Warnings and Precautions (5.2) | 1/2026
Warnings and Precautions (5.3, 5.5) | 8/2025

1 INDICATIONS AND USAGE

BRIUMVI is a CD20-directed cytolytic antibody indicated for the treatment of relapsing forms of multiple sclerosis (MS), to include clinically isolated syndrome, relapsing-remitting disease, and active secondary progressive disease, in adults (1, 14).

2 DOSAGE AND ADMINISTRATION

- Before initiating BRIUMVI, screen for Hepatitis B virus (HBV) and obtain serum quantitative immunoglobulins, aminotransferases, alkaline phosphatase, and bilirubin (2.1).
- Pre-medicate with methylprednisolone (or an equivalent corticosteroid) and an antihistamine (e.g., diphenhydramine) prior to each infusion (2.2).
- Administer BRIUMVI by intravenous infusion.
  - First Infusion: 150 mg intravenous infusion (2.3)
  - Second Infusion: 450 mg intravenous infusion two weeks after the first infusion (2.3)
  - Subsequent Infusions: 450 mg intravenous infusion 24 weeks after the first infusion and every 24 weeks thereafter (2.3)
- Must be diluted in 0.9% Sodium Chloride Injection, USP prior to administration (2.3, 2.6).
- Monitor patients closely during and for at least one hour after the completion of the first two infusions. Post-infusion monitoring of subsequent infusions is at physician discretion unless infusion reaction and/or hypersensitivity has been observed (2.3, 5.1).

3 DOSAGE FORMS AND STRENGTHS

Injection: 150 mg/6 mL (25 mg/mL) in a single-dose vial (3)

4 CONTRAINDICATIONS

- Active hepatitis B virus infection (4)
- History of life-threatening infusion reaction to BRIUMVI (4)

5 WARNINGS AND PRECAUTIONS

- Infusion Reactions: Management recommendations for infusion reactions depend on the type and severity of the reaction. Permanently discontinue BRIUMVI if a life-threatening or disabling infusion reaction occurs (2.3, 5.1).
- Infections: Serious, including life-threatening and fatal infections, have occurred. Delay BRIUMVI administration in patients with an active infection until the infection is resolved. Vaccination with live-attenuated or live vaccines is not recommended during treatment with BRIUMVI and after discontinuation, until B-cell repletion (5.2).
- Reduction in Immunoglobulins: Monitor the level of immunoglobulins at the beginning, during, and after discontinuation of treatment with BRIUMVI, until B-cell repletion, and especially when recurrent serious infections are suspected. Consider discontinuing BRIUMVI in patients with serious opportunistic or recurrent serious infections, and if prolonged hypogammaglobulinemia requires treatment with intravenous immunoglobulins (2.1, 5.4).
- Fetal Risk: May cause fetal harm based on animal data. Advise females of reproductive potential of the potential risk to a fetus and to use effective contraception during treatment and for at least 6 months after stopping BRIUMVI (5.3, 8.1, 8.3).
- Liver Injury: Clinically significant liver injury has occurred. Obtain serum aminotransferases, alkaline phosphatase, and bilirubin levels before initiating BRIUMVI, and during treatment as clinically indicated. Discontinue BRIUMVI in patients with evidence of liver injury in the absence of an alternative etiology (5.5).

6 ADVERSE REACTIONS

The most common adverse reactions (≥10%) were infusion reactions and upper respiratory tract infections (6.1).

To report SUSPECTED ADVERSE REACTIONS, contact TG Therapeutics at 1-877-848-9462 or FDA at 1-800-FDA-1088 or www.fda.gov/medwatch.

FULL PRESCRIBING INFORMATION

1 INDICATIONS AND USAGE

BRIUMVI is indicated for the treatment of relapsing forms of multiple sclerosis (MS), to include clinically isolated syndrome, relapsing-remitting disease, and active secondary progressive disease, in adults.

2 DOSAGE AND ADMINISTRATION

2.1 Assessments Prior to First Dose of BRIUMVI

Hepatitis B Virus Screening

Prior to initiating BRIUMVI, perform Hepatitis B virus (HBV) screening. BRIUMVI is contraindicated in patients with active HBV confirmed by positive results for Hepatitis B surface antigen [HBsAg] and anti-HBV tests. For patients who are negative for HBsAg and positive for Hepatitis B core antibody [HBcAb+] or are carriers of HBV [HBsAg+], consult liver disease experts before starting and during treatment with BRIUMVI [see Warnings and Precautions (5.2)] .

Serum Immunoglobulins

Prior to initiating BRIUMVI, perform testing for quantitative serum immunoglobulins [see Warnings and Precautions (5.4)]. For patients with low serum immunoglobulins, consult immunology experts before initiating treatment with BRIUMVI.

Vaccinations

Because vaccination with live-attenuated or live vaccines is not recommended during treatment and after discontinuation until B-cell repletion, administer all immunizations according to immunization guidelines at least 4 weeks prior to initiation of BRIUMVI for live or live-attenuated vaccines and, whenever possible, at least 2 weeks prior to initiation of BRIUMVI for non-live vaccines [see Warnings and Precautions (5.2)and Clinical Pharmacology (12.2)] .

Liver Function Tests

Prior to initiating BRIUMVI, obtain serum aminotransferases (alanine aminotransferase [ALT] and aspartate aminotransferase [AST]), alkaline phosphatase, and bilirubin levels [see Warnings and Precautions (5.5)] .

2.2 Assessment and Premedication Before Every Infusion

Infection Assessment

Prior to every infusion of BRIUMVI, determine whether there is an active infection. In case of active infection, delay infusion of BRIUMVI until the infection resolves [see Warnings and Precautions (5.2)] .

Recommended Premedication

Pre-medicate with 100 mg of methylprednisolone administered intravenously (or an equivalent oral dosage or equivalent corticosteroid) approximately 30 minutes prior to each BRIUMVI infusion to reduce the frequency and severity of infusion reactions [see Warnings and Precautions (5.1)] . Pre-medicate with an antihistamine (e.g., diphenhydramine) administered orally or intravenously approximately 30-60 minutes prior to each BRIUMVI infusion to further reduce the frequency and severity of infusion reactions.

The addition of an antipyretic (e.g., acetaminophen) may also be considered.

2.3 Recommended Dosage and Dose Administration

Administer BRIUMVI under the close supervision of an experienced healthcare professional with access to appropriate medical support to manage severe reactions, such as serious infusion reactions.

- First Infusion: 150 mg intravenous infusion
- Second Infusion: 450 mg intravenous infusion administered two weeks after the first infusion
- Subsequent Infusions: 450 mg intravenous infusion administered 24 weeks after the first infusion and every 24 weeks thereafter
- Observe the patient for at least one hour after the completion of the first two infusions. Post-infusion monitoring of subsequent infusions is at physician discretion unless infusion reaction and/or hypersensitivity has been observed in association with the current or any prior infusion [see Warnings and Precautions (5.1)].

Table 1: Recommended Dose, Infusion Rate, and Infusion Duration for MS
 | Dose (mg) and Volume (mL) of BRIUMVI | Volume (mL) of 0.9% Sodium Chloride Injection, USP [Withdraw and discard the required volume of 0.9% Sodium Chloride Injection, USP from the infusion bag following the preparation instructions in Preparation and Administration (2.6).] | Infusion Rate (mL/hour) | Duration [Infusion duration may take longer if the infusion is interrupted or slowed.]
First Infusion | 150 mg (6 mL) | 250 mL | - Start at 10 mL per hour for the first 30 minutes - Increase to 20 mL per hour for the next 30 minutes - Increase to 35 mL per hour for the next hour - Increase to 100 mL per hour for the remaining 2 hours | 4 hours
Second Infusion (2 weeks later) | 450 mg (18 mL) | 250 mL | - Start at 100 mL per hour for the first 30 minutes - Increase to 400 mL per hour for the remaining 30 minutes | 1 hour
Subsequent Infusions (once every 24 weeks) [Administer the first subsequent infusion 24 weeks after the first infusion.] | 450 mg (18 mL) | 250 mL | - Start at 100 mL per hour for the first 30 minutes - Increase to 400 mL per hour for the remaining 30 minutes | 1 hour

2.4 Delayed or Missed Doses

If a planned infusion of BRIUMVI is missed, administer BRIUMVI as soon as possible; do not wait until the next scheduled infusion. Reset the infusion schedule to administer the next sequential infusion 24 weeks after the missed infusion is administered. Infusions of BRIUMVI must be separated by at least 5 months.

2.5 Dosage Modifications Because of Infusion Reactions

Dose modifications in response to infusion reactions depend on the severity.

Life-Threatening Infusion Reactions

Immediately stop infusion and permanently discontinue BRIUMVI if there are signs of a life-threatening or disabling infusion reaction [see Warnings and Precautions (5.1)] . Provide appropriate supportive treatment.

Severe Infusion Reactions

Immediately interrupt the infusion and administer appropriate supportive treatment, as necessary [see Warnings and Precautions (5.1)] . Restart the infusion only after all symptoms have resolved. When restarting, begin at half of the infusion rate at the time of onset of the infusion reaction [see Dosage and Administration (2.3)] . If this rate is tolerated, increase the rate as described in Table 1. This change in rate will increase the total duration of the infusion but not the total dose.

Mild to Moderate Infusion Reactions

Reduce the infusion rate to half the rate at the onset of the infusion reaction and maintain the reduced rate for at least 30 minutes [see Warnings and Precautions (5.1)] . If the reduced rate is tolerated, increase the rate as described in Table 1. This change in rate will increase the total duration of the infusion but not the total dose.

2.6 Preparation and Administration

Preparation

Only use 0.9% Sodium Chloride Injection, USP to dilute BRIUMVI.

BRIUMVI must be prepared by a healthcare professional using aseptic technique. Prepare the solution for infusion as follows:

- BRIUMVI should be a clear to opalescent, colorless to slightly yellow solution. Parenteral drug products should be inspected visually for particulate matter and discoloration prior to administration, whenever solution and container permit. Do not use the solution if discolored or if the solution contains discrete foreign particulate matter.

Preparation of Solution for First Infusion:

- Prepare infusion bag for First Infusion (150 mg) using one vial (150 mg/6 mL) of BRIUMVI.
- Withdraw 6 mL 0.9% Sodium Chloride Injection, USP from the 250 mL infusion bag and discard.
- Withdraw 6 mL BRIUMVI solution from the vial.
- Add 6 mL (150 mg) BRIUMVI into the infusion bag containing 0.9% Sodium Chloride Injection, USP.

Preparation of Solution for Second Infusion and Subsequent Infusions:

- Prepare infusion bag for Second Infusion (450 mg) and Subsequent Infusions (450 mg) using three vials (150 mg/6 mL) of BRIUMVI.
- Withdraw 18 mL 0.9% Sodium Chloride Injection, USP from the 250 mL infusion bag and discard.
- Withdraw 18 mL BRIUMVI solution from the vials (6 mL/vial).
- Add 18 mL (450 mg) BRIUMVI into the infusion bag containing 0.9% Sodium Chloride Injection, USP.

Mix diluted solution by gentle inversion. Do not shake.

Administration of Infusion Solution

Prior to the start of the intravenous infusion, the contents of the infusion bag should be at room temperature [see Dosage and Administration (2.7)] .

Administer the diluted infusion solution through a dedicated line.

No incompatibilities between BRIUMVI and polyvinyl chloride (PVC) or polyolefin (PO) bags and intravenous (IV) administration sets have been observed.

2.7 Storage Instructions for the Prepared Infusion Solution

Use the prepared infusion solution immediately. If the diluted solution is not administered immediately, store refrigerated at 2°C to 8°C (36°F to 46°F) for up to 24 hours. Do not freeze. If the diluted solution is stored refrigerated, allow it to equilibrate to room temperature prior to administration (approximately 2 hours). The diluted solution can be stored for an additional 8 hours at room temperature up to 25°C (77°F), which includes the equilibration time and infusion time.

3 DOSAGE FORMS AND STRENGTHS

Injection: 150 mg/6 mL (25 mg/mL) clear to opalescent, colorless to slightly yellow solution in a single-dose vial.

4 CONTRAINDICATIONS

BRIUMVI is contraindicated in patients with:

- Active HBV infection [see Dosage and Administration (2.1)and Warnings and Precautions (5.2)]
- A history of life-threatening infusion reaction to BRIUMVI [see Warnings and Precautions (5.1)]

5 WARNINGS AND PRECAUTIONS

5.1 Infusion Reactions

BRIUMVI can cause infusion reactions, which can include pyrexia, chills, headache, influenza-like illness, tachycardia, nausea, throat irritation, erythema, and an anaphylactic reaction [see Adverse Reactions (6.1)] . In Studies 1 and 2 [see Clinical Studies (14)] , patients received methylprednisolone (or an equivalent steroid), an antihistamine, and possibly other pre-medication (i.e., acetaminophen) to reduce the risk of infusion reactions prior to each infusion. The incidence of infusion reactions in Studies 1 and 2 in patients who received treatment with BRIUMVI was 48%, with the highest incidence within 24 hours of the first infusion. In Studies 1 and 2, there were no fatal infusion reactions, but 0.6% of patients treated with BRIUMVI experienced infusion reactions that were serious, some requiring hospitalization.

Observe patients treated with BRIUMVI for infusion reactions during the infusion and for at least one hour after the completion of the first two infusions. Post-infusion monitoring of subsequent infusions is at physician discretion unless infusion reaction and/or hypersensitivity has been observed in association with the current or any prior infusion. Inform patients that infusion reactions can occur up to 24 hours after the infusion.

Reducing the Risk of Infusion Reactions and Managing Infusion Reactions

Administer pre-medication (e.g., methylprednisolone or an equivalent corticosteroid, and an antihistamine) to reduce the frequency and severity of infusion reactions [see Dosage and Administration (2.2)] . The addition of an antipyretic (e.g., acetaminophen) may also be considered [see Dosage and Administration (2.2)].

Management recommendations for infusion depend on the type and severity of the reaction. For life-threatening infusion reactions, stop the infusion immediately, permanently discontinue BRIUMVI, and provide appropriate supportive treatment [see Dosage and Administration (2.5)] . For less severe infusion reactions, management may involve temporarily stopping the infusion, reducing the infusion rate, and/or administering symptomatic treatment.

5.2 Infections

Serious, including life-threatening or fatal, bacterial and viral infections have been reported in patients receiving BRIUMVI. An increased risk of infections, including serious and fatal bacterial, fungal, and new or reactivated viral infections, has been observed during and following completion of treatment with other anti-CD20 B-cell depleting therapies.

In Studies 1 and 2, the overall rate of infections in MS patients treated with BRIUMVI was 56% compared to 54% in patients who were treated with teriflunomide. The rate of serious infections was higher in patients treated with BRIUMVI compared to patients treated with teriflunomide (5% vs 3%, respectively). There were 3 infection-related deaths that occurred in controlled clinical trials in patients with relapsing forms of multiple sclerosis (RMS), all in patients treated with BRIUMVI; the infections leading to death were post-measles encephalitis, pneumonia, and post-operative salpingitis following an ectopic pregnancy. In Studies 1 and 2, the most common infections reported in patients treated with BRIUMVI included upper respiratory tract infection (45%) and urinary tract infection (10%).

Delay BRIUMVI administration in patients with an active infection until the infection is resolved.

Possible Increased Risk of Immunosuppressant Effects with Other Immunosuppressants

When initiating BRIUMVI after an immunosuppressive therapy or initiating an immunosuppressive therapy after BRIUMVI, consider the potential for increased immunosuppressive effects [see Drug Interactions (7.1)and Clinical Pharmacology (12.2)] . BRIUMVI has not been studied in combination with other MS therapies.

Hepatitis B Virus (HBV) Reactivation

HBV reactivation occurred in an MS patient treated with BRIUMVI in clinical trials. Fulminant hepatitis, hepatic failure, and death caused by HBV reactivation have occurred in patients treated with anti-CD20 antibodies.

Perform HBV screening in all patients before initiation of treatment with BRIUMVI. Do not start treatment with BRIUMVI in patients with active HBV confirmed by positive results for HBsAg and anti-HB tests. For patients who are negative for surface antigen [HBsAg] and positive for HB core antibody [HBcAb+] or are carriers of HBV [HBsAg+], consult a liver disease expert before starting and during treatment.

Progressive Multifocal Leukoencephalopathy (PML)

PML is an opportunistic viral infection of the brain caused by the JC virus (JCV) that typically only occurs in patients who are immunocompromised, and that usually leads to death or severe disability. JCV infection resulting in PML has been observed in patients treated with anti-CD20 antibodies, including BRIUMVI, and other MS therapies. At the first sign or symptom suggestive of PML, withhold BRIUMVI and perform an appropriate diagnostic evaluation. Typical symptoms associated with PML are diverse, progress over days to weeks, and include progressive weakness on one side of the body or clumsiness of limbs, disturbance of vision, and changes in thinking, memory, and orientation leading to confusion and personality changes.

Magnetic resonance imaging (MRI) findings may be apparent before clinical signs or symptoms. Cases of PML, diagnosed based on MRI findings and the detection of JCV DNA in the cerebrospinal fluid in the absence of clinical signs or symptoms specific to PML, have been reported in patients treated with other MS medications associated with PML. Many of these patients subsequently became symptomatic with PML. Therefore, monitoring with MRI for signs that may be consistent with PML may be useful, and any suspicious findings should lead to further investigation to allow for an early diagnosis of PML, if present. Following discontinuation of another MS medication associated with PML, lower PML-related mortality and morbidity have been reported in patients who were initially asymptomatic at diagnosis compared to patients who had characteristic clinical signs and symptoms at diagnosis.

It is not known whether these differences are due to early detection and discontinuation of MS treatment or due to differences in disease in these patients.

If PML is confirmed, treatment with BRIUMVI should be discontinued.

Vaccinations

Administer all immunizations according to immunization guidelines at least 4 weeks prior to initiation of BRIUMVI for live or live-attenuated vaccines and, whenever possible, at least 2 weeks prior to initiation of BRIUMVI for non-live vaccines.

BRIUMVI may interfere with the effectiveness of non-live vaccines.

The safety of immunization with live or live-attenuated vaccines during or following administration of BRIUMVI has not been studied. Vaccination with live virus vaccines is not recommended during treatment with BRIUMVI and until B-cell repletion.

Vaccination of Infants Born to Mothers Treated with BRIUMVI During Pregnancy

In infants of mothers exposed to BRIUMVI during pregnancy, do not administer live or live-attenuated vaccines before confirming the recovery of B-cell counts as measured by CD19^+B-cells. Depletion of B-cells in these infants may increase the risks from live or live-attenuated vaccines.

Inactivated or non-live vaccines may be administered as indicated, prior to recovery from B-cell depletion, but an assessment of vaccine immune responses, including consultation with a qualified specialist, should be considered to determine whether a protective immune response was mounted [see Use in Specific Populations (8.1)] .

5.3 Fetal Risk

Based on data from animal studies, BRIUMVI may cause fetal harm when administered to a pregnant woman. Transient peripheral B-cell depletion and lymphocytopenia have been reported in infants born to mothers exposed to other anti-CD20 B-cell depleting antibodies during pregnancy. Advise females of reproductive potential to use effective contraception during BRIUMVI treatment and for 6 months after the last dose [see Use in Specific Populations (8.1, 8.3)] .

5.4 Reduction in Immunoglobulins

As expected with any B-cell depleting therapy, decreased immunoglobulin levels were observed with BRIUMVI. Decrease in immunoglobulin M (IgM) was reported in 0.6% of patients treated with BRIUMVI compared to none of the patients treated with teriflunomide in RMS clinical trials [see Adverse Reactions (6.1)] . No decline in immunoglobulin G (IgG) was observed at the end of the studies. Data from clinical studies using other anti-CD20 monoclonal antibody therapies have shown an association between decreased levels of immunoglobulin M (IgM< lower limit of normal [LLN]) and G (IgG<LLN) and increased rates of serious infections. Monitor the levels of quantitative serum immunoglobulins during treatment, especially in patients with opportunistic or recurrent infections, and after discontinuation of therapy until B-cell repletion. Consider discontinuing BRIUMVI therapy if a patient with low immunoglobulins develops a serious opportunistic infection or recurrent infections, or if prolonged hypogammaglobulinemia requires treatment with intravenous immunoglobulins.

5.5 Liver Injury

Clinically significant liver injury, without findings of viral hepatitis, has been reported in the postmarketing setting in patients treated with anti-CD20 B-cell depleting therapies approved for the treatment of MS, including BRIUMVI. Signs of liver injury, including markedly elevated serum hepatic enzymes with elevated total bilirubin, have occurred from weeks to months after administration.

Patients treated with BRIUMVI found to have an alanine aminotransaminase (ALT) or aspartate aminotransferase (AST) greater than 3× the upper limit of normal (ULN) with serum total bilirubin greater than 2× ULN are potentially at risk for severe drug-induced liver injury.

Obtain liver function tests prior to initiating treatment with BRIUMVI [see Dosage and Administration (2.1)] , and monitor for signs and symptoms of any hepatic injury during treatment. Measure serum aminotransferases, alkaline phosphatase, and bilirubin levels promptly in patients who report symptoms that may indicate liver injury, including new or worsening fatigue, anorexia, nausea, vomiting, right upper abdominal discomfort, dark urine, or jaundice. If liver injury is present and an alternative etiology is not identified, discontinue BRIUMVI.

6 ADVERSE REACTIONS

The following serious adverse reactions are discussed in greater detail in other sections of the labeling:

- Infusion Reactions [see Warnings and Precautions (5.1)]
- Infections [see Warnings and Precautions (5.2)]
- Reduction in Immunoglobulins [see Warnings and Precautions (5.4)]
- Liver Injury [see Warnings and Precautions (5.5)]

6.1 Clinical Trials Experience

Because clinical trials are conducted under widely varying conditions, adverse reaction rates observed in the clinical trials of a drug cannot be directly compared to rates in the clinical trials of another drug and may not reflect the rates observed in clinical practice.

In active-controlled clinical trials (Study 1 and Study 2), 545 patients with RMS received BRIUMVI [see Clinical Studies (14)].

The most common adverse reactions in RMS trials (incidence of at least 10%) were infusion reactions and upper respiratory tract infections. Table 2 summarizes the adverse reactions that occurred in RMS trials (Study 1 and Study 2). The most common cause of discontinuation in patients treated with BRIUMVI was infection (1.3%).

Table 2: Adverse Reactions in Adult Patients with RMS with an Incidence of at least 5% for BRIUMVI and Higher than Teriflunomide from Study 1 and Study 2
 | BRIUMVI 450 mg IV [The first dose of BRIUMVI was given as an intravenous (IV) infusion of 150 mg. The second dose was given as an IV infusion of 450 mg two weeks after the first infusion.] | Teriflunomide 14 mg PO
Adverse Reactions | (N=545) % | (N=548) %
Infusion reactions | 48 | 12
Upper respiratory tract infections [Includes the following: nasopharyngitis, upper respiratory tract infection, respiratory tract infection, respiratory tract infection viral, pharyngitis, rhinitis, sinusitis, acute sinusitis, tonsillitis, laryngitis, chronic sinusitis, viral pharyngitis, viral rhinitis, viral upper respiratory tract infection, chronic tonsillitis, pharyngitis streptococcal, sinusitis bacterial, and tonsillitis bacterial.] | 45 | 41
Lower respiratory tract infections [Includes the following: bronchitis, pneumonia, tracheitis, tracheobronchitis, COVID-19 pneumonia, bronchitis bacterial, and pneumonia viral.] | 9 | 7
Herpes virus-associated infections [Includes several related terms.] | 6 | 5
Pain in extremity | 6 | 4
Insomnia | 6 | 3
Fatigue | 5 | 4

Infusion Reactions

The incidence of infusion reactions was highest with the first infusion (43%), decreasing with subsequent infusions (10% with second, 8% with third infusion). Three (0.6%) patients treated with BRIUMVI reported serious infusion reactions. Most frequently reported symptoms (greater than 5%) included pyrexia, chills, headache, and influenza-like illness [see Warnings and Precautions (5.1)] .

Laboratory Abnormalities

Decreased Immunoglobulins

BRIUMVI decreased total immunoglobulins with the greatest decline seen in IgM levels. The proportion of BRIUMVI-treated patients at baseline reporting IgG, IgA, and IgM below the LLN was 6.3%, 0.6%, and 1.1%, respectively. Following treatment, the proportion of BRIUMVI-treated patients reporting IgG, IgA, and IgM below the LLN at 96 weeks was 6.5%, 2.4%, and 20.9%, respectively.

Decreased Neutrophil Levels

In Studies 1 and 2, decreased neutrophil counts (<LLN) occurred in 15% of BRIUMVI-treated patients compared to 22% in teriflunomide-treated patients. The majority of decreased neutrophil counts were observed once for a given patient treated with BRIUMVI, and were between 1.0 and 1.5 × 10^9/L. In RMS studies, 3% of patients in the BRIUMVI group had neutrophil counts less than 1.0 × 10^9/L, compared to 2% of patients in the teriflunomide group. Overall, 1% of patients in the BRIUMVI group had neutrophil counts less than 0.5 × 10^9/L, compared to 0% of patients in the teriflunomide group, and these were not associated with an infection.

6.2 Postmarketing Experience

The following adverse reactions have been identified during postapproval use of BRIUMVI. Because these reactions are reported voluntarily from a population of uncertain size, it is not always possible to reliably estimate their frequency or establish a causal relationship to drug exposure.

Hepatobiliary Disorders: Liver injury [see Warnings and Precautions (5.5)]

Infections and Infestations: Progressive multifocal leukoencephalopathy [see Warnings and Precautions (5.2)]

7 DRUG INTERACTIONS

7.1 Immunosuppressive or Immune-Modulating Therapies

The concomitant usage of BRIUMVI with other immune-modulating or immunosuppressant drugs, including immunosuppressant doses of corticosteroids, may increase the risk of infection. Consider the risk of additive immune system effects when co-administering immunosuppressive therapies with BRIUMVI.

When switching from therapies with immune effects, the duration and mechanism of action of these therapies should be taken into account because of potential additive immunosuppressive effects when initiating BRIUMVI.

8 USE IN SPECIFIC POPULATIONS

8.1 Pregnancy

Pregnancy Exposure Registry

There is a pregnancy exposure registry that monitors pregnancy outcomes in women exposed to BRIUMVI during pregnancy. Eligible patients are women who become pregnant either while taking BRIUMVI or within 6 months following their last dose of BRIUMVI. Physicians are encouraged to register patients and pregnant women are encouraged to register themselves by calling 1-877-411-4546 or visiting www.briumvipregnancyregistry.com.

Risk Summary

There are no data on the developmental risk associated with the use of BRIUMVI in pregnant women. Data from case reports of pregnancies occurring during clinical trials with BRIUMVI are insufficient to identify a drug-associated risk of major birth defects, miscarriage, or adverse maternal or fetal outcomes. Although there are no data on ublituximab-xiiy, monoclonal antibodies can be actively transported across the placenta, and BRIUMVI may cause immunosuppression in the in-uteroexposed infant [see Clinical Considerations, Warnings and Precautions (5.2, 5.3), and Clinical Pharmacology (12.1, 12.2)].

In pregnant transgenic huCD20 mice, a pharmacologically relevant animal model, weekly intravenous administration of ublituximab-xiiy during organogenesis resulted in no adverse pregnancy or embryofetal outcomes (see Data) .

The estimated background risk of major birth defects and miscarriage for the indicated population is unknown. All pregnancies have a background risk of birth defect, loss, or other adverse outcomes. In the U.S. general population, the estimated background risk of major birth defects and miscarriage in clinically recognized pregnancies is 2% to 4% and 15% to 20%, respectively.

Clinical Considerations

Fetal/Neonatal Adverse Reactions

Transport of endogenous IgG antibodies across the placenta increases as pregnancy progresses and peaks during the third trimester. There are no data on B-cell levels in human neonates following maternal exposure to BRIUMVI. However, transient peripheral B-cell depletion and lymphocytopenia have been reported in infants born to mothers exposed to other anti-CD20 antibodies during pregnancy. Avoid administering live vaccines to neonates and infants exposed to BRIUMVI in uterountil B-cell recovery occurs [see Warnings and Precautions (5.2)and Clinical Pharmacology (12.2)].

Data

Animal Data

Weekly intravenous administration of ublituximab-xiiy (0 or 30 mg/kg) to pregnant monkeys during the first, second, or third trimester of pregnancy produced a severe immunogenic response in dams, resulting in maternal morbidity and death and embryofetal loss. Dosing was terminated in dams after only two doses during the third trimester because of multiple deaths in dams dosed during the first and second trimesters.

External, visceral, and skeletal abnormalities occurred in two infants from dams exposed during the second trimester of pregnancy. Histopathology evaluations revealed minimal to moderate degeneration/necrosis in the brain. Findings in infants included contractures and abnormal flexion of multiple limbs and tail, shortened mandible, elongate calvarium, enlargement of ears, and/or craniomandibular abnormalities which were attributed to brain necrosis. The findings in cynomolgus monkey were considered secondary to an immunogenic reaction and are not considered relevant to humans.

In a subsequent study conducted in pregnant CD20 (huCD20) transgenic mice, a pharmacologically relevant animal model, intravenous administration of ublituximab-xiiy (0, 5, 20, or 50 mg/kg) during organogenesis (gestation day 6 and 12) resulted in no adverse effects on embryofetal development. There was a marked reduction in B-cells in fetal blood at all but the lowest dose tested.

8.2 Lactation

Risk Summary

There are no data on the presence of ublituximab-xiiy in human milk, the effects on the breastfed infant, or the effects of the drug on milk production. Human IgG is excreted in human milk, and the potential for absorption of ublituximab-xiiy to lead to B-cell depletion in the infant is unknown. The developmental and health benefits of breastfeeding should be considered along with the mother's clinical need for BRIUMVI and any potential adverse effects on the breastfed infant from BRIUMVI or from the underlying maternal condition.

8.3 Females and Males of Reproductive Potential

Contraception

Females

Females of reproductive potential should use effective contraception while receiving BRIUMVI and for 6 months after the last dose of BRIUMVI [see Warnings and Precautions (5.3)and Use in Specific Populations (8.1)] .

8.4 Pediatric Use

Safety and effectiveness in pediatric patients have not been established.

8.5 Geriatric Use

Clinical studies of BRIUMVI did not include sufficient numbers of patients 65 years of age and older to determine whether they respond differently from younger adult patients.

11 DESCRIPTION

Ublituximab-xiiy is a recombinant chimeric monoclonal IgG1 antibody with reduced fucose content directed against CD20-expressing B-cells. The molecular weight of the antibody is approximately 147 kDa.

BRIUMVI (ublituximab-xiiy) injection for intravenous infusion is a sterile, clear to opalescent, colorless to slightly yellow, preservative-free solution. Each mL of solution contains 25 mg ublituximab-xiiy, 0.4 mg hydrochloric acid, 0.7 mg polysorbate 80, 9.0 mg sodium chloride, 6.4 mg sodium citrate, and Water for Injection, USP. The pH is 6.5.

12 CLINICAL PHARMACOLOGY

12.1 Mechanism of Action

The precise mechanism by which ublituximab-xiiy exerts its therapeutic effects in multiple sclerosis is unknown, but is presumed to involve binding to CD20, a cell surface antigen present on pre-B and mature B lymphocytes. Following cell surface binding to B lymphocytes, ublituximab-xiiy results in cell lysis through mechanisms including antibody-dependent cellular cytolysis and complement-dependent cytolysis.

12.2 Pharmacodynamics

For B-cell counts, assays for CD19^+B-cells are used because the presence of ublituximab-xiiy interferes with the CD20 assay. Treatment with BRIUMVI reduced CD19^+B-cell counts in blood by the first measured timepoint of 24 hours after infusion. In clinical studies (Study 1 and Study 2), B-cell counts rose to above the LLN or above baseline counts between infusions of BRIUMVI at least one time in 30 of 545 (5.5%) of patients. The median time for CD19^+B-cell counts to return to either baseline or LLN was 70.3 weeks (range 0.1-75.1 weeks) after the last BRIUMVI infusion. Within 1.5 years after the last infusion, B-cell counts rose to either baseline or LLN in 58% of patients.

12.3 Pharmacokinetics

Ublituximab-xiiy exposures increased proportionally over a dose range of 150 mg (0.33 times approved recommended dosage) to 600 mg (1.33 times the approved recommended dosage) in patients with RMS.

Following administration of the approved recommended dosage of BRIUMVI, the geometric mean steady-state AUC was 3000 mcg/mL per day (CV=28%) and the mean maximum concentration was 139 mcg/mL (CV=15%).

Distribution

The estimated central volume of distribution of ublituximab-xiiy was 3.18 L.

Elimination

The estimated mean terminal half-life of ublituximab-xiiy was 22 days.

Metabolism

Ublituximab-xiiy is a protein for which the expected metabolic pathway is degradation to small peptides and amino acids by ubiquitous proteolytic enzymes.

Specific Populations

There were no clinically meaningful differences in the pharmacokinetics of ublituximab-xiiy based on age, sex, body weight, anti-drug antibodies (ADAs) presence, mild renal impairment, or mild hepatic impairment. The effect of moderate to severe renal impairment or moderate to severe hepatic impairment on the pharmacokinetics of ublituximab-xiiy is unknown.

Drug Interaction Studies

No studies evaluating the drug interaction potential of ublituximab-xiiy have been conducted.

12.6 Immunogenicity

The observed incidence of ADAs is highly dependent on the sensitivity and specificity of the assay. Differences in assay methods preclude meaningful comparisons of the incidence of ADAs in the studies described below with the incidence of ADAs in other studies, including those of ublituximab-xiiy or of other ublituximab products.

In clinical studies (Study 1 and Study 2), serum samples from patients with RMS were tested for antibodies to ublituximab-xiiy during the 96-week treatment period. Of the 534 BRIUMVI-treated patients, 434 (81%) tested positive for ADAs at one or more timepoints, and 34 (6.4%) tested positive for neutralizing antibodies (NAbs). However, the assay used to measure NAbs is subject to interference from serum ublituximab-xiiy, possibly resulting in underestimation of the incidence of NAb formation and limiting the ability to characterize the clinical impact of NAbs.

The presence of ADAs had no observable impact on the safety or efficacy of BRIUMVI.

13 NONCLINICAL TOXICOLOGY

13.1 Carcinogenesis, Mutagenesis, Impairment of Fertility

Carcinogenesis

No carcinogenicity studies have been conducted to assess the carcinogenic potential of BRIUMVI.

Mutagenesis

As an antibody, BRIUMVI is not expected to interact directly with DNA.

Impairment of Fertility

No studies in animals have been conducted to assess the effects of BRIUMVI on male or female fertility. No adverse effects on male or female reproductive organs were observed at the only dose level evaluated (30 mg/kg) in a 26-week intravenous toxicity study in monkeys, which was associated with plasma exposures (Cave) approximately 24 times that in humans at the maximum recommended human dose (450 mg).

14 CLINICAL STUDIES

The efficacy of BRIUMVI was demonstrated in two randomized, double-blind, double-dummy, parallel group, active comparator-controlled clinical trials of identical design, in patients with RMS treated for 96 weeks [Study 1 (NCT03277261) and Study 2 (NCT03277248)]. Patients were randomized to receive either BRIUMVI, given as an IV infusion of 150 mg for the first infusion, 450 mg two weeks after the first infusion for the second infusion/second dose, and 450 mg every 24 weeks after the first infusion for subsequent doses (third infusion and beyond) with oral placebo administered daily; or teriflunomide, the active comparator, given orally as a 14 mg daily dose with IV placebo administered on the same schedule as BRIUMVI. Both studies enrolled patients who had experienced at least one relapse in the previous year, two relapses in the previous two years, or had the presence of a T1 gadolinium (Gd)-enhancing lesion in the previous year. Patients were also required to have an Expanded Disability Status Scale (EDSS) score from 0 to 5.5 at baseline. Neurological evaluations were performed at baseline, every 12 weeks, and at the time of a suspected relapse. Brain MRI scans were performed at baseline and at Weeks 12, 24, 48, and 96.

The primary outcome of both Study 1 and Study 2 was the annualized relapse rate (ARR) over the treatment period. Additional outcome measures included: the total number of MRI T1 Gd-enhancing lesions by Week 96, the total number of new or enlarging MRI T2 hyperintense lesions by Week 96, and time to confirmed disability progression for at least 12 weeks. Disability progression was defined as an increase of greater than or equal to 1.0 point from the baseline EDSS score that was attributable to MS when the baseline score was 5.5 or less, and greater than or equal to 0.5 points when the baseline score was above 5.5. Confirmed disability progression was evaluated in a pooled analysis of Studies 1 and 2. Disability progression was considered confirmed when the increase in the EDSS was confirmed at a regularly scheduled visit 12 weeks after the initial documentation of neurological worsening.

In Study 1, 274 patients were randomized to BRIUMVI and 275 to teriflunomide. Of those randomized to BRIUMVI, 88% completed the 96-week treatment period; of those randomized to teriflunomide, 92% completed the 96-week treatment period. The baseline demographic and disease characteristics were balanced between the two treatment groups. At baseline, the mean age was 37 years, 97% were White, and 63% were female.

In Study 2, 272 patients were randomized to BRIUMVI and 273 to teriflunomide. Of those randomized to BRIUMVI, 93% completed the 96-week treatment period; of those randomized to teriflunomide, 88% completed the 96-week treatment period. The baseline demographic and disease characteristics were balanced between the two treatment groups. At baseline, the mean age was 35 years, 99% were White, and 65% were female.

In Study 1 and Study 2, BRIUMVI significantly lowered the ARR compared to teriflunomide. BRIUMVI statistically significantly reduced the number of T1 Gd-enhancing lesions and the number of new or enlarging T2 lesions in both studies compared to teriflunomide. There was no statistically significant difference in disability progression confirmed at 12 weeks between BRIUMVI-treated and teriflunomide-treated patients.

Results for Study 1 and Study 2 are presented in Table 3.

Table 3: Key Clinical and MRI Endpoints in RMS Patients from Study 1 and Study 2
 |  | Study 1 |  | Study 2
Endpoints |  | BRIUMVI 450 mg [BRIUMVI dosing by intravenous infusion: first dose of 150 mg, second dose 450 mg two weeks after the first; subsequent doses 450 mg every 24 weeks; teriflunomide dosing: 14 mg by mouth once daily.] | Teriflunomide 14 mg | BRIUMVI 450 mg | Teriflunomide 14 mg
Clinical Endpoints [Based on Modified Intent-to-Treat (mITT) Population, defined as all randomized patients who received at least one infusion of study medication and had one baseline and post-baseline efficacy assessment. Study 1: BRIUMVI (N=271), teriflunomide (N=274). Study 2: BRIUMVI (N=272), teriflunomide (N=272).]
Annualized Relapse Rate (Primary Endpoint) |  | 0.076 | 0.188 | 0.091 | 0.178
 | Relative Reduction | 59% (p<0.001) |  | 49% (p = 0.002)
Proportion of Patients with 12-week Confirmed Disability Progression [Data prospectively pooled from Study 1 and Study 2: BRIUMVI (N=543), teriflunomide (N=546).] , [Defined as an increase of 1.0 point or more from the baseline EDSS score for patients with baseline score of 5.5 or less, or 0.5 point or more when the baseline score is greater than 5.5, Kaplan-Meier estimates at Week 96.] |  | 5.2% BRIUMVI vs. 5.9% teriflunomide
 | Risk Reduction (Pooled Analysis) [Based on Hazard Ratio.] | 16% (p = 0.510)
MRI Endpoints [Based on MRI-mITT population (mITT patients who have baseline and post-baseline MRI). Study 1: BRIUMVI (N=265), teriflunomide (N=270). Study 2: BRIUMVI (N=272), teriflunomide (N=267).]
Mean number of T1 Gd-enhancing lesions per MRI [At Week 96.] |  | 0.016 | 0.491 | 0.009 | 0.250
 | Relative Reduction | 97% (p<0.001) |  | 97% (p<0.001)
Mean number of new or enlarging T2 hyperintense lesions per MRI |  | 0.213 | 2.789 | 0.282 | 2.831
 | Relative Reduction | 92% (p<0.001) |  | 90% (p<0.001)

In exploratory analyses of Study 1 and Study 2, a similar effect of BRIUMVI on the ARR was observed in subgroups defined by gender, prior non-steroid MS therapy, baseline disability (EDSS 3.5 or lower versus greater than 3.5), the number of relapses in the 2 years prior to study enrollment, and number of Gd-enhancing lesions at baseline.

16 HOW SUPPLIED/STORAGE AND HANDLING

16.1 How Supplied

BRIUMVI (ublituximab-xiiy) injection is a sterile, clear to opalescent, colorless to slightly yellow, preservative-free solution for intravenous use supplied as a carton containing one 150 mg/6 mL (25 mg/mL) single-dose vial (NDC 73150-150-06).

16.2 Storage and Handling

Store BRIUMVI vials refrigerated at 2°C to 8°C (36°F to 46°F) in the outer carton to protect from light. Do not freeze. Do not shake.

17 PATIENT COUNSELING INFORMATION

Advise the patient to read the FDA-approved patient labeling (Medication Guide).

Infusion Reactions

Inform patients about the signs and symptoms of infusion reactions and that infusion reactions can occur up to 24 hours after infusion. Advise patients to contact their healthcare provider immediately for signs or symptoms of infusion reactions [see Warnings and Precautions (5.1)] .

Infection

Advise patients to contact their healthcare provider for any signs of infection during treatment or after the last infusion. Signs can include fever, chills, constant cough, or dysuria [see Warnings and Precautions (5.2)] .

Advise patients that BRIUMVI may cause reactivation of hepatitis B infection and that monitoring will be required if they are at risk [see Warnings and Precautions (5.2)] .

Advise patients that PML has happened with BRIUMVI. Inform the patient that PML is characterized by a progression of deficits and usually leads to death or severe disability over weeks or months. Instruct the patient of the importance of contacting their doctor if they develop any symptoms suggestive of PML. Inform the patient that typical symptoms associated with PML are diverse, progress over days to weeks, and include progressive weakness on one side of the body or clumsiness of limbs, disturbance of vision, and changes in thinking, memory, and orientation leading to confusion and personality changes [see Warnings and Precautions (5.2)] .

Vaccination

Advise patients to complete any required live or live-attenuated vaccinations at least 4 weeks and, whenever possible, non-live vaccinations at least 2 weeks prior to initiation of BRIUMVI. Administration of live-attenuated or live vaccines is not recommended during BRIUMVI treatment and until B-cell recovery [see Warnings and Precaution (5.2)] .

Fetal Risk

Advise pregnant women and females of reproductive potential of the potential risk to a fetus. Advise females of reproductive potential to use effective contraception during treatment with BRIUMVI and for 6 months after the last BRIUMVI dose. Advise patients to notify their healthcare provider if they are pregnant or plan to become pregnant during treatment with BRIUMVI [see Warnings and Precautions (5.3)and Use in Specific Populations (8.1, 8.3)] .

Pregnancy Registry

Instruct patients that if they are pregnant or plan to become pregnant while taking BRIUMVI they should inform their healthcare provider [see Use in Specific Populations (8.1)] .

Encourage patients to enroll in the BRIUMVI Pregnancy Registry if they become pregnant while taking BRIUMVI or within 6 months following the last dose of BRIUMVI [see Use in Specific Populations (8.1)] .

Liver Injury

Inform patients that liver injury has been reported with anti-CD20 B-cell depleting therapies, including BRIUMVI. Instruct patients treated with BRIUMVI to promptly report any symptoms that may indicate liver injury, including fatigue, anorexia, nausea, vomiting, right upper abdominal discomfort, dark urine, or jaundice. A blood test should be obtained before patients start therapy, and during treatment as clinically indicated [see Warnings and Precautions (5.5)] .

Manufactured by:
TG Therapeutics, Inc.
3020 Carrington Mill Blvd
Morrisville, NC 27560
U.S. License No. 2090

BRIUMVI is a registered trademark of TG Therapeutics, Inc.

©TG Therapeutics, Inc. 2021-2022, 2024. All rights reserved.

MEDICATION GUIDE
BRIUMVI® (bree-UM-vee)
(ublituximab-xiiy)
injection,
for intravenous use

What is the most important information I should know about BRIUMVI?
BRIUMVI can cause serious side effects, including:

- Infusion reactions.Infusion reactions are one of the most common side effects of BRIUMVI. Infusion reactions can be serious and may require you to be hospitalized. You will be monitored during your infusion and may be monitored after each infusion of BRIUMVI for signs and symptoms of an infusion reaction. Tell your healthcare provider if you get any of these symptoms:

- fever
- chills
- headache
- flu-like symptoms
- fast heartbeat
- hives

- itchy skin
- dizziness
- feeling faint
- swelling of tongue or throat
- trouble breathing

- wheezing
- nausea
- abdominal pain
- throat irritation
- redness of the face or skin

These infusion reactions can happen over 24 hours after your infusion.It is important that you call your healthcare provider right away if you get any of the signs or symptoms listed above after each infusion. If you get an infusion reaction, your healthcare provider may need to stop or slow down the rate of your infusion.

- Infections.Infections are a common side effect, and upper respiratory tract infections are one of the most common side effects of BRIUMVI .BRIUMVI increases your risk of getting infections caused by bacteria or viruses that may be life-threatening or cause death. Tell your healthcare provider if you have an infection or have any of the following signs of infection including fever, chills, a cough that does not go away, or painful urination. Your healthcare provider should delay your treatment with BRIUMVI until your infection is gone.
  - Hepatitis B virus (HBV) reactivation:Before starting treatment with BRIUMVI, your healthcare provider will do blood tests to check for hepatitis B viral infection. If you have ever had hepatitis B virus infection, the hepatitis B virus may become active again during or after treatment with BRIUMVI. Hepatitis B virus becoming active again (called reactivation) may cause serious liver problems including liver failure or death. Your healthcare provider will monitor you if you are at risk for hepatitis B virus reactivation during treatment and after you stop receiving BRIUMVI.
  - Weakened immune system:BRIUMVI taken before or after other medicines that weaken the immune system could increase your risk of getting infections.
  - Progressive Multifocal Leukoencephalopathy (PML):PML has happened with BRIUMVI. PML is a rare, serious brain infection caused by a virus that may get worse over days or weeks. PML can result in death or severe disability. Tell your healthcare provider right away if you have any new or worsening neurologic signs or symptoms. These symptoms may include weakness on one side of your body, loss of coordination in arms and legs, vision problems, changes in thinking and memory which may lead to confusion, and personality changes.
- Low immunoglobulins.BRIUMVI may cause a decrease in some types of antibodies. Your healthcare provider will do blood tests to check your blood immunoglobulin levels.

What is BRIUMVI?
BRIUMVI is a prescription medicine used to treat adults with relapsing forms of multiple sclerosis (MS), including:

- clinically isolated syndrome
- relapsing-remitting disease
- active secondary progressive disease

It is not known if BRIUMVI is safe or effective in children.

Do not receive BRIUMVI if you:

- have active hepatitis B virus (HBV) infection.
- have had a life-threatening allergic reaction to BRIUMVI. Tell your healthcare provider if you have had an allergic reaction to BRIUMVI. See " What are the ingredients in BRIUMVI?" for a complete list of ingredients in BRIUMVI.

Before receiving BRIUMVI, tell your healthcare provider about all of your medical conditions, including if you:

- have or think you have an infection. See " What is the most important information I should know about BRIUMVI?"
- take or plan to take medicines that affect your immune system. These medicines may increase your risk of getting an infection.
- have ever had hepatitis B or are a carrier of the hepatitis B virus.
- have a history of liver problems.
- have had a recent vaccination or are scheduled to receive any vaccinations.
  - You should receive any required 'live' or 'live-attenuated' vaccines at least 4 weeks before you start treatment with BRIUMVI.You should not receive'live' or 'live-attenuated' vaccines while you are being treated with BRIUMVI and until your healthcare provider tells you that your immune system is no longer weakened.
  - When possible, you should receive any 'non-live' vaccines at least 2 weeks before you start treatment with BRIUMVI.If you would like to receive any non-live vaccines while you are being treated with BRIUMVI, talk to your healthcare provider.
  - If you have a baby and you received BRIUMVI during your pregnancy, it is important to tell your baby's healthcare provider about receiving BRIUMVI so they can decide when your baby should be vaccinated.
- are pregnant, think that you might be pregnant, or plan to become pregnant. It is not known if BRIUMVI will harm your unborn baby. You should use birth control (contraception) during treatment with BRIUMVI and for at least 6 months after your last infusion of BRIUMVI. Talk with your healthcare provider about what birth control method is right for you during this time.
  - Pregnancy Registry. There is a pregnancy registry for women who take BRIUMVI during pregnancy. If you become pregnant while receiving BRIUMVI or within 6 months following the last dose of BRIUMVI, tell your healthcare provider right away. Talk to your healthcare provider about registering with the BRIUMVI Pregnancy Registry. The purpose of this registry is to collect information about your health and your baby's health. Either you or your healthcare provider can enroll you in this registry by calling 1-877-411-4546 or visiting www.briumvipregnancyregistry.com.
- are breastfeeding or plan to breastfeed. It is not known if BRIUMVI passes into your breast milk. Talk to your healthcare provider about the best way to feed your baby if you take BRIUMVI.

Tell your healthcare provider about all the medicines you take,including prescription and over-the-counter medicines, vitamins, and herbal supplements.

How will I receive BRIUMVI?

- BRIUMVI is given through a needle placed in your vein (intravenous infusion) in your arm.
- Before treatment with BRIUMVI, you will receive a corticosteroid and an antihistamine medicine to help reduce the risk of infusion reactions by making them less frequent and less severe. You may also receive other medicines to help reduce the risk of an infusion reaction. See " What is the most important information I should know about BRIUMVI?"
- Your first dose of BRIUMVI will last about 4 hours.
- Your second dose of BRIUMVI will be given 2 weeks after your first dose. This infusion will last about 1 hour.
- Your next doses of BRIUMVI will be given as 1 infusion every 24 weeks. These infusions will last about 1 hour.

What are the possible side effects of BRIUMVI?
BRIUMVI may cause serious side effects, including:

- See " What is the most important information I should know about BRIUMVI?"
- Liver damage.BRIUMVI may cause liver damage. Your healthcare provider will do blood tests to check your liver before you start BRIUMVI and while you take BRIUMVI if needed. Tell your healthcare provider right away if you have any symptoms of liver damage, such as:
  - yellowing of the skin and eyes (jaundice)
  - nausea
  - vomiting
  - unusual darkening of the urine
  - feeling tired or weak

The most common side effects of BRIUMVI include:

- Infusion reactions, upper and lower respiratory tract infections, herpes infections, extremity pain, insomnia, and fatigue. See " What is the most important information I should know about BRIUMVI?"

These are not all the possible side effects of BRIUMVI. Call your doctor for medical advice about side effects.
You may report side effects to FDA at 1-800-FDA-1088.

General information about the safe and effective use of BRIUMVI.
Medicines are sometimes prescribed for purposes other than those listed in a Medication Guide. You can ask your pharmacist or healthcare provider for information about BRIUMVI that is written for health professionals.

What are the ingredients in BRIUMVI?
Active ingredient: ublituximab-xiiy.
Inactive ingredients:hydrochloric acid, polysorbate 80, sodium chloride, sodium citrate, Water for Injection, USP.
BRIUMVI is a registered trademark of TG Therapeutics, Inc.
©TG Therapeutics, Inc. 2021-2022, 2024. All rights reserved.
Manufactured by: TG Therapeutics, Inc., 3020 Carrington Mill Blvd, Morrisville, NC 27560
U.S. License No. 2090
For more information, go to www.briumvi.com or call 1-877-848-9462

This Medication Guide has been approved by the U.S. Food and Drug Administration

Revised: 1/2026

PRINCIPAL DISPLAY PANEL

NDC 73150-150-06

Briumvi™

(ublituximab-xiiy) injection

150 mg/6 mL

(25 mg/mL)

For Intravenous Infusion

After Dilution.

Discard Unused Portion.

Attention: Dispense the enclosed Medication
Guide to each patient.

Rx only

Contains one 6 mL
single-dose vial.

TG Therapeutics

PRINCIPAL DISPLAY PANEL

NDC 73150-150-06

Briumvi™

(ublituximab-xiiy) injection

Rx only

150 mg/6 mL (25 mg/mL)

For Intravenous Infusion After Dilution.

Single-Dose Vial. Discard Unused Portion.

No preservative. Dosage:

See prescribing information.

TG Therapeutics